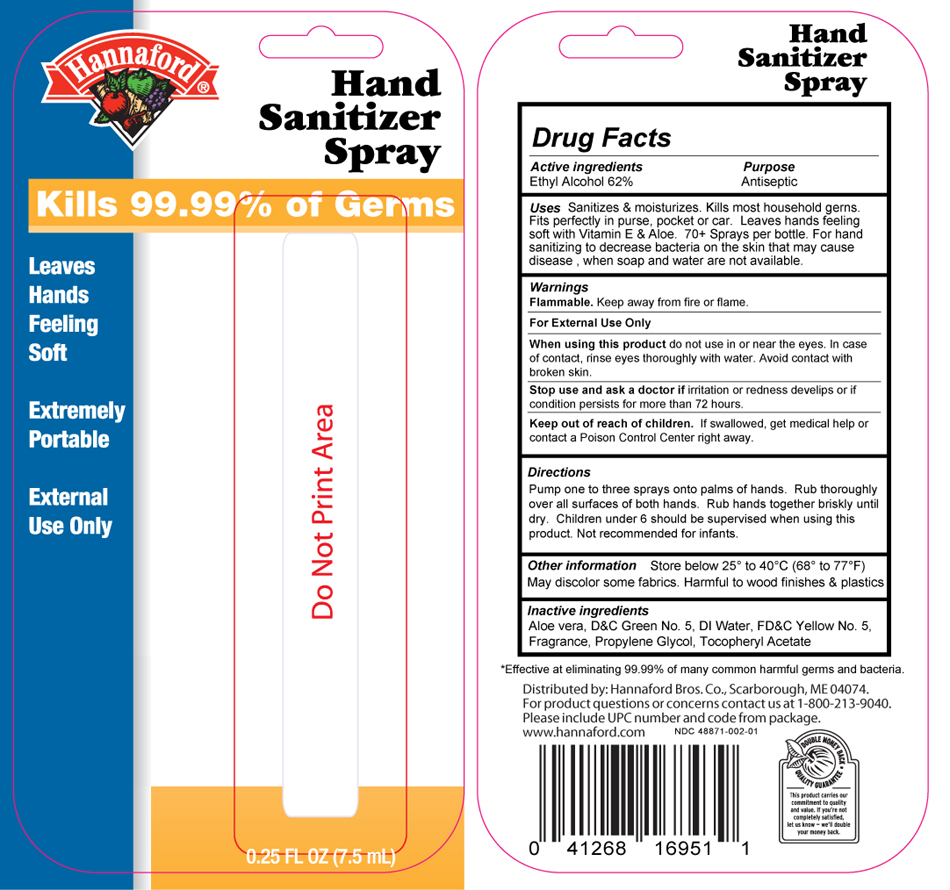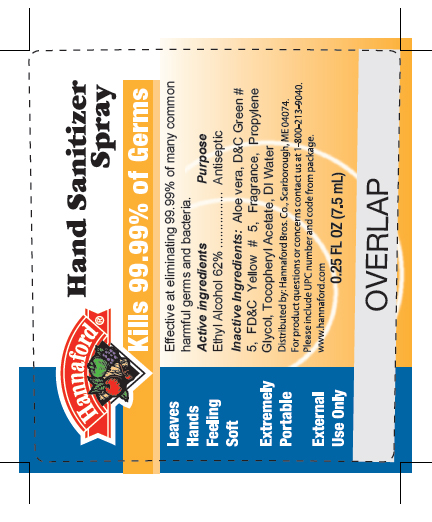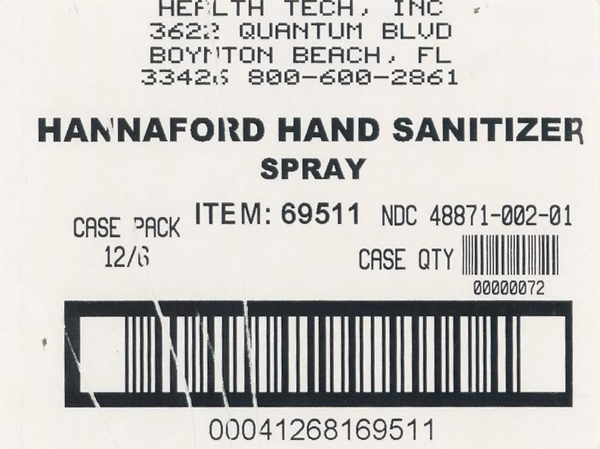 DRUG LABEL: Hannaford Hand Sanitizer 
NDC: 48871-002 | Form: SPRAY
Manufacturer: Health-Tech, Inc.
Category: otc | Type: HUMAN OTC DRUG LABEL
Date: 20100323

ACTIVE INGREDIENTS: alcohol 4.65 mL/7.5 mL
INACTIVE INGREDIENTS: aloe vera leaf; ALPHA-TOCOPHEROL ACETATE; Propylene Glycol; water

Drug Facts

Active Ingredient

Ethyl alcohol

Purpose

Antiseptic

Uses

- For hand sanitizing to decrease bacteria on the skin.

- Recommended for repeated use.

Warnings

- For external use only.
- Do not use in eye area.

Flammable: Keep away from heat or flame.

When using this product

- Keep out of eyes. In case of eye contact, flush eyes thoroughly with water.
- Avoid contact with broken skin.

Stop use and ask a doctor if

Irritation or redness develops or if condition persists for more than 72 hours.

Keep out of reach of children

If swallowed, get medical help, or contact a Poison control Center immediately.

Directions

- Pump one to three sprays onto palms of hands
- Rub thoroughly over all surfaces of both hands
- Rub hands together briskly until dry
- Children under 6 should be supervised when using this product
- Not recommended for infants

Other information

- Store at 20^0 to 25^0 C (68^0 to 77^0 F)
- Prior to initial use, prime pump by depressing multiple times
- May discolor certain fabrics
- harmful to wood finishes and plastics

Inactive Ingredients

Aloe Vera, D and C Green 5, DI Water, FD and C Yellow 5, Fragrance, Propylene Glycol, Tocopheryl Acetate

Hannaford bottle label

MM9

Hannaford blister card

MM10

Hannaford shipper label

MM11